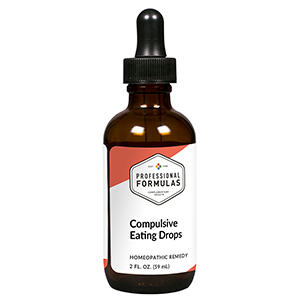 DRUG LABEL: Compulsive Eating Drops
NDC: 63083-2073 | Form: LIQUID
Manufacturer: Professional Complementary Health Formulas
Category: homeopathic | Type: HUMAN OTC DRUG LABEL
Date: 20190815

ACTIVE INGREDIENTS: GARCINIA GUMMI-GUTTA FRUIT 2 [hp_X]/59 mL; ARTEMISIA CINA PRE-FLOWERING TOP 3 [hp_X]/59 mL; FUCUS VESICULOSUS 3 [hp_X]/59 mL; MEDICAGO SATIVA WHOLE 3 [hp_X]/59 mL; AMMONIUM CARBONATE 6 [hp_X]/59 mL; PHOSPHORUS 6 [hp_X]/59 mL; PHYTOLACCA AMERICANA ROOT 6 [hp_X]/59 mL; LYCOPODIUM CLAVATUM SPORE 6 [hp_X]/59 mL; THYROID, UNSPECIFIED 6 [hp_X]/59 mL; ANTIMONY TRISULFIDE 8 [hp_X]/59 mL; AMMONIUM BROMIDE 12 [hp_X]/59 mL; SULFUR 12 [hp_X]/59 mL; OYSTER SHELL CALCIUM CARBONATE, CRUDE 20 [hp_X]/59 mL; SCABIES LESION LYSATE (HUMAN) 30 [hp_X]/59 mL
INACTIVE INGREDIENTS: ALCOHOL; WATER

C73

ACTIVE INGREDIENTS

Garcinia cambogia 2X
Cina 3X
Fucus vesiculosus 3X
Medicago sativa 3X
Ammonium carbonicum 6X
Phosphorus 6X
Phytolacca decandra 6X
Lycopodium clavatum 6X, 12X
Thyroid 6X, 12X
Antimonium crudum 8X
Ammonium bromatum 12X
Sulphur 12X, 30X
Calcarea carbonica 20X
Psorinum 30X

QUESTIONS

Professional Formulas

PO Box 2034 Lake Oswego, OR 97035

INDICATIONS

Temporarily reduces cravings related to compulsive overeating or binge eating.*

PURPOSE

*Claims based on traditional homeopathic practice, not accepted medical evidence. Not FDA evaluated.

WARNINGS

Consult a doctor if symptoms persist. Keep out of the reach of children. In case of overdose, get medical help or contact a poison control center right away. If pregnant or breastfeeding, ask a healthcare professional before use.

Keep out of the reach of children.

PREGNANCY OR BREAST FEEDING

If pregnant or breastfeeding, ask a healthcare professional before use.

DIRECTIONS

Place drops under tongue 30 minutes before/after meals. Adults and children 12 years and over: Take 10 drops up to 3 times per day for up to 6 weeks. For immediate onset of symptoms, take 10 to 15 drops every 15 minutes up to 3 hours. For less severe symptoms, take 10-15 drops hourly up to 8 hours. Consult a physician for use in children under 12 years of age.

OTHER INFORMATION

Tamper resistant. If seal is broken, do not use. After opening, close container tightly and store at room temperature away from heat.

INACTIVE INGREDIENTS

20% ethanol, purified water.

LABEL

Est 1985

Professional Formulas

Complementary Health

Compulsive Eating Drops

Homeopathic Remedy

2 FL. OZ. (59 mL)